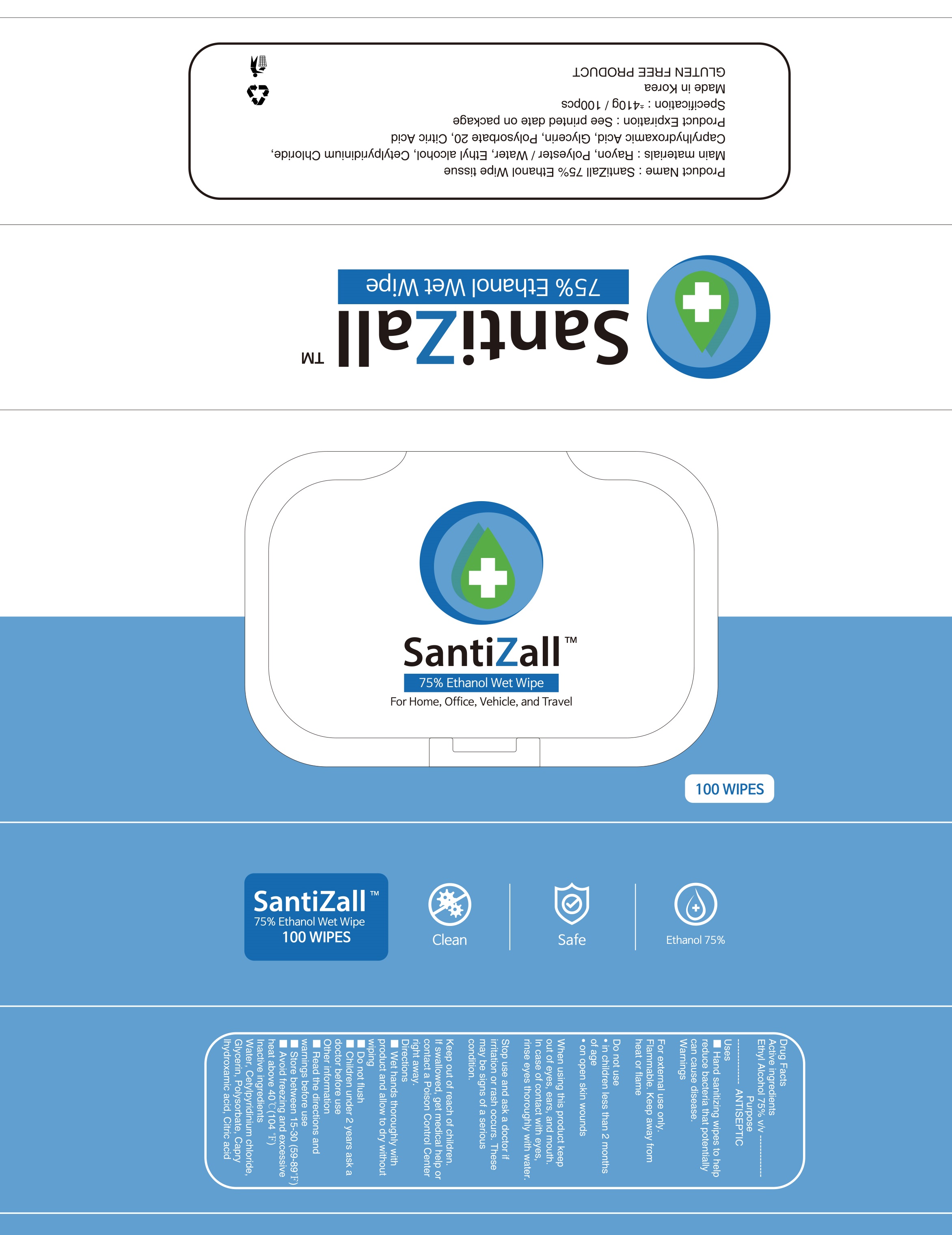 DRUG LABEL: SantiZall 75 percent Ethanol Wet Wipe
NDC: 78580-020 | Form: CLOTH
Manufacturer: Glory Co., Ltd.
Category: otc | Type: HUMAN OTC DRUG LABEL
Date: 20200616

ACTIVE INGREDIENTS: ALCOHOL 75 1/100 1
INACTIVE INGREDIENTS: WATER; CETYLPYRIDINIUM CHLORIDE; Glycerin; CAPRYLHYDROXAMIC ACID; CITRIC ACID MONOHYDRATE

Drug Facts

ACTIVE INGREDIENT

Ethyl Alcohol 75% v/v

INACTIVE INGREDIENTS

Water, Cetylpyridinium chloride, Glycerin, Polysorbate, Caprylhydroxamic acid, Citric acid

PURPOSE

ANTISEPTIC

WARNINGS

For external use only. Flammable. Keep away from heat or flame
--------------------------------------------------------------------------------------------------------
Do not use
• in children less than 2 months of age
• on open skin wounds
--------------------------------------------------------------------------------------------------------
When using this product keep out of eyes, ears, and mouth. In case of contact with eyes, rinse eyes thoroughly with water.
--------------------------------------------------------------------------------------------------------
Stop use and ask a doctor if irritation or rash occurs. These may be signs of a serious condition.

KEEP OUT OF REACH OF CHILDREN

If swallowed, get medical help or contact a Poison Control Center right away.

Uses

Hand sanitizing wipes to help reduce bacteria that potentially can cause disease.

Directions

■ Wet hands thoroughly with product and allow to dry without wiping
■ Do not flush
■ Children under 2 years ask a doctor before use

Other information

■ Read the directions and warnings before use
■ Store between 15-30℃(59-89℉)
■ Avoid freezing and excessive heat above 40℃(104 ℉)